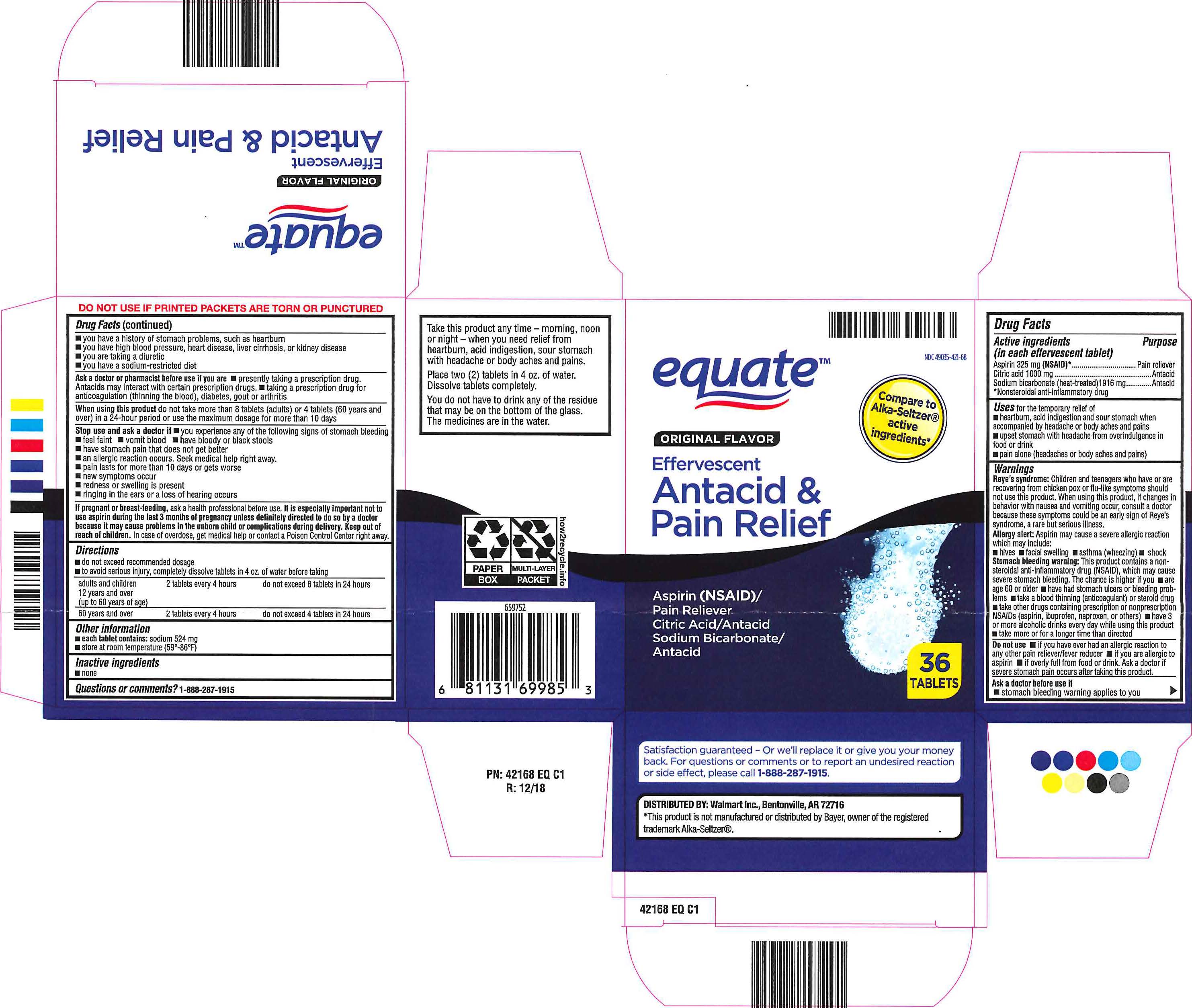 DRUG LABEL: Equate Effervescent Antacid and Pain Relief
NDC: 49035-421 | Form: TABLET, EFFERVESCENT
Manufacturer: Walmart
Category: otc | Type: HUMAN OTC DRUG LABEL
Date: 20251017

ACTIVE INGREDIENTS: ASPIRIN 325 mg/1 1; SODIUM BICARBONATE 1916 mg/1 1; ANHYDROUS CITRIC ACID 1000 mg/1 1

Equate Effervescent Antacid & Pain Relief

Active ingredients

(in each effervescent tablet)

Aspirin 325 mg (NSAID)*

Citric acid 1000 mg

Sodium bicarbonate (heat-treated) 1916 mg

*Nonsteroidal anti-inflammatory drug

Purpose

Aspirin 325 mg (NSAID)*. . . . . . . . . . . . . . . . . . . . . .Pain reliever

Citric acid 1000 mg . . . . . . . . . . . . . . . . . . . . . .. . . . Antacid

Sodium bicarbonate (heat-treated) 1916 mg . . . . . . Antacid

*Nonsteroidal anti-inflammatory drug

Uses

Uses for the temporary relief of

■ heartburn, acid indigestion and sour stomach when accompanied by headache or body aches and pains

■ upset stomach with headache from overindulgence in food or drink

■ pain alone (headaches or body aches and pains)

Warnings

Reye’s syndrome: Children and teenagers who have or are recovering from chicken pox or flu-like symptoms should not use this product. When using this product, if changes in behavior with nausea and vomiting occur, consult a doctor because these symptoms could be an early sign of Reye’s syndrome, a rare but serious illness.

Allergy alert: Aspirin may cause a severe allergic reaction which may include: ■ hives ■ facial swelling ■ asthma (wheezing) ■ shock

Stomach bleeding warning: This product contains a nonsteroidal anti-inflammatory drug (NSAID), which may cause severe stomach bleeding. The chance is higher if you ■ are age 60 or older ■ have had stomach ulcers or bleeding problems ■ take a blood thinning (anticoagulant) or steroid drug ■ take other drugs containing prescription or nonprescription NSAIDs (aspirin, ibuprofen, naproxen, or others) ■ have 3 or more alcoholic drinks every day while using this product ■ take more or for a longer time than directed

Do not use ■ if you have ever had an allergic reaction to any other pain reliever/fever reducer

■ if you are allergic to aspirin ■ if overly full from food or drink. Ask a doctor if severe stomach pain occurs after taking this product.

Ask a doctor before use if ■ stomach bleeding warning applies to you ■ you have a history of stomach problems, such as heartburn ■ you have high blood pressure, heart disease, liver cirrhosis, or kidney disease ■ you are taking a diuretic ■ you have a sodium-restricted diet

Ask a doctor or pharmacist before use if you are ■ presently taking a prescription drug. Antacids may interact with certain prescription drugs. ■ taking a prescription drug for anticoagulation (thinning the blood), diabetes, gout or arthritis

When using this product do not take more than 8 tablets (adults) or 4 tablets (60 years and over) in a 24-hour period or use the maximum dosage for more than 10 days

Stop use and ask a doctor if ■ you experience any of the following signs of stomach bleeding

■ feel faint ■ vomit blood ■ have bloody or black stools ■ have stomach pain that does not get better

■ an allergic reaction occurs. Seek medical help right away.

■ pain lasts for more than 10 days or gets worse ■ new symptoms occur

■ redness or swelling is present ■ ringing in the ears or a loss of hearing occurs

If pregnant or breast-feeding, ask a health professional before use. It is especially important not to use aspirin during the last 3 months of pregnancy unless definitely directed to do so by a doctor because it may cause problems in the unborn child or complications during delivery.

Keep out of reach of children.

In case of overdose,get medical help or contact a Poison Control Center right away.

Directions

■ do not exceed recommended dosage

■ to avoid serious injury, completely dissolve tablets in 4oz. of water before taking

adults and children 12 years and over (up to 60 years of age): 2 tablets every 4 hours - do not exceed 8 tablets in 24 hours

60 years and over: 2 tablets every 4 hours - do not exceed 4 tablets in 24 hours

Take this product any time - morning, noon or night - when you need relief from heartburn, acid indigestion, sour stomach with headache or body aches and pains.

Place two (2) tablets in 4 oz. of water. Dissolve tablets completely. You do not have to drink any of the residue that may be on the bottom of the glass. The medicienes are in the water.

Other information

■ each tablet contains: sodium 524 mg

■ store at room temperature (59-86ºF)

Inactive ingredients

■ none

Questions or comments?

1-888-287-1915